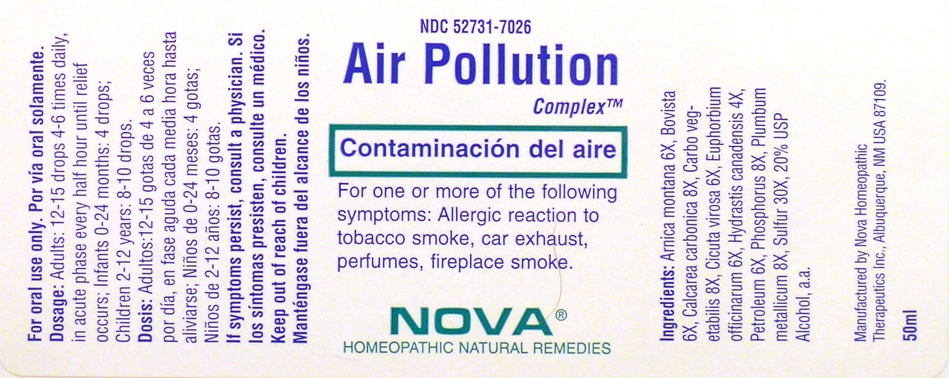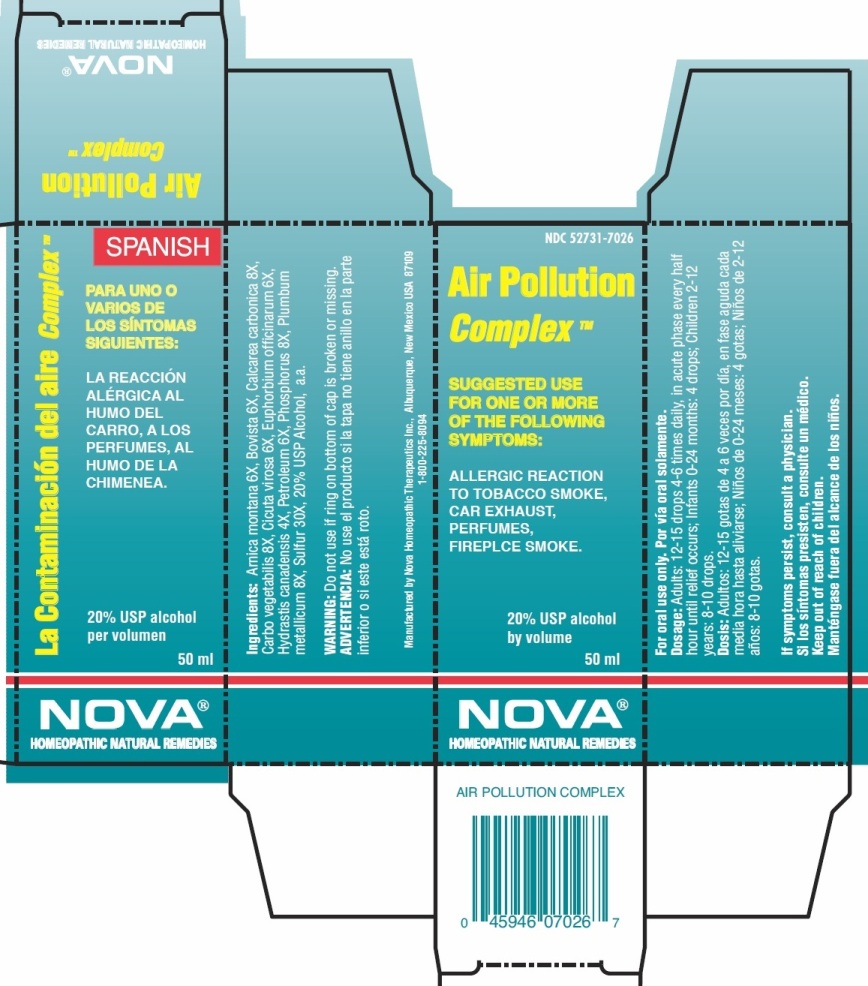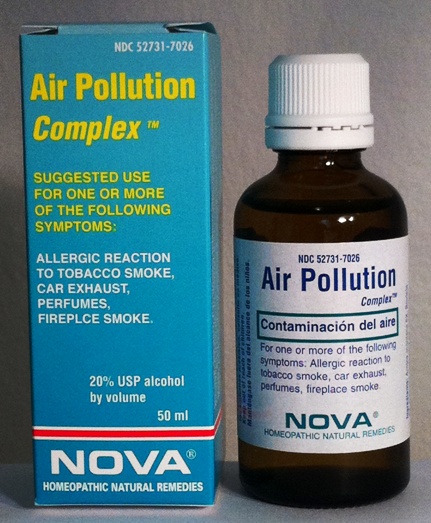 DRUG LABEL: Air Pollution Complex
NDC: 52731-7026 | Form: LIQUID
Manufacturer: Nova Homeopathic Therapeutics, Inc.
Category: homeopathic | Type: HUMAN OTC DRUG LABEL
Date: 20110601

ACTIVE INGREDIENTS: ARNICA MONTANA 6 [hp_X]/1 mL; GIANT PUFFBALL 6 [hp_X]/1 mL; OYSTER SHELL CALCIUM CARBONATE, CRUDE 8 [hp_X]/1 mL; ACTIVATED CHARCOAL 8 [hp_X]/1 mL; CICUTA VIROSA ROOT 6 [hp_X]/1 mL; EUPHORBIA RESINIFERA RESIN 6 [hp_X]/1 mL; GOLDENSEAL 4 [hp_X]/1 mL; LIQUID PETROLEUM 6 [hp_X]/1 mL; PHOSPHORUS 8 [hp_X]/1 mL; LEAD 8 [hp_X]/1 mL; SULFUR 30 [hp_X]/1 mL
INACTIVE INGREDIENTS: ALCOHOL 10 mL/50 mL

Air Pollution Complex

Purpose:

Suggested use for one or more of the following symptoms:

Allergic reaction to tobacco smoke, car exhaust, perfumes, fireplace smoke.

Usage and Dosage:

For oral use only.

DOSAGE AND ADMINISTRATION

Adults:
In Accute Phase:
12-15 drops, every half hour until relief occurs
When Relief Occurs:
12-15 drops, 4-6 times daily
Children 2-12 years:
8-10 drops, 4-6 times daily
Infants 0-24 months:
4 drops, 4-6 times daily

Warnings:

Keep out of reach of children.

WARNINGS

If symptoms persist, consult a physician.

Do not use if ring on bottom of cap is broken or missing.

Active Ingredients:

Arnica montana 6X, Bovista 6X, Calcarea carbonica 8X,
Carbo vegetabilis 8X, Cicuta virosa 6X, Euphorbium officinarum 6X,
Hydrastis canadensis 4X, Petroleum 6X, Phosphorus 8X, Plumbum
metallicum 8X, Sulfur 30X

Inactive Ingredients:

Alcohol, 20% USP

QUESTIONS

Manufactured by Nova Homeopathic Therapeutics Inc., Albuquerque, New Mexico USA 87109
1-800-225-8094

PACKAGE LABEL

Air Pollution Complex Product
Air Pollution Complex Bottle Label
Air Pollution Complex Box